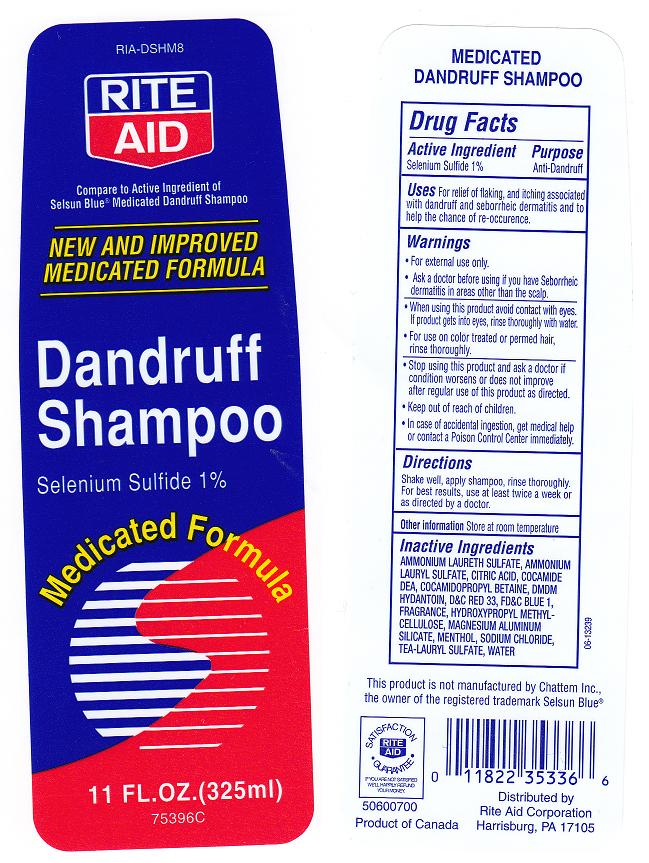 DRUG LABEL: Rite Aid
NDC: 11822-6101 | Form: SHAMPOO
Manufacturer: Rite Aid Corporation
Category: otc | Type: HUMAN OTC DRUG LABEL
Date: 20100929

ACTIVE INGREDIENTS: SELENIUM SULFIDE 1 mL/100 mL
INACTIVE INGREDIENTS: WATER; AMMONIUM LAURYL SULFATE; TROLAMINE LAURYL SULFATE; AMMONIUM LAURETH-5 SULFATE; COCAMIDOPROPYL BETAINE; MAGNESIUM ALUMINUM SILICATE; MENTHOL; COCO DIETHANOLAMIDE; DMDM HYDANTOIN; CITRIC ACID MONOHYDRATE; HYDROXYPROPYL CELLULOSE; SODIUM CHLORIDE; SODIUM CITRATE; D&C RED NO. 33; FD&C BLUE NO. 1

Drug Facts Box - Back Label

ACTIVE INGREDIENT

SELENIUM SULFIDE 1%

PURPOSE

- ANTI DANDRUFF

WARNINGS

- FOR EXTERNAL USE ONLY.

ASK A DOCTOR BEFORE USING IF YOU HAVE

SEBORRHEIC DERMATITIS IN AREAS OTHER THAN THE SCALP

WHEN USING THIS PRODUCT

- AVOID CONTACT WITH THE EYES. IF CONTACT OCCURS, RINSE EYES THOROUGHLY WITH WATER. FOR USE ON COLOR-TREATED OR PERMED HAIR, RINSE THOROUGHLY.

STOP USE AND ASK A DOCTOR IF

- CONDITION WORSENS OR DOES NOT IMPROVE AFTER REGULAR USE OF THIS PRODUCT AS DIRECTED.

KEEP OUT OF REACH OF CHILDREN

- IF SWALLOWED, GET MEDICAL HELP OR CONTACT A POISON CONTROL CENTER RIGHT AWAY.

USE

FOR RELIEF OF FLAKING AND ITCHING DUE TO DANDRUFF, AND SEBORRHEIC DERMATITIS, AND TO HELP PREVENT THE CHANCE OF RE-OCCURRENCE.

DIRECTIONS

- SHAKE WELL, SHAMPOO, THEN RINSE THROUGHLY.
- FOR BEST RESULTS, USE AT LEAST TWICE A WEEK OR AS DIRECTED BY A DOCTOR.

INACTIVE INGREDIENTS

WATER, AMMONIUM LAURYL SULFATE, TEA-LAURYL SULFATE, AMMONIUM LAURETH SULFATE, COCAMIDOPROPYL BETAINE, MAGNESIUM ALUMINUM SILICATE, FRAGRANCE, MENTHOL, COCAMIDE DEA, DMDM HYDANTOIN, CITRIC ACID, HYDROXYPROPYL METHYLCELLULOSE, SODIUM CITRATE, SODIUM CHLORIDE, BLUE 1 (CI 42090), RED 33 (CI 17200)

PACKAGE FRONT AND BACK LABELS

eql11.jpg